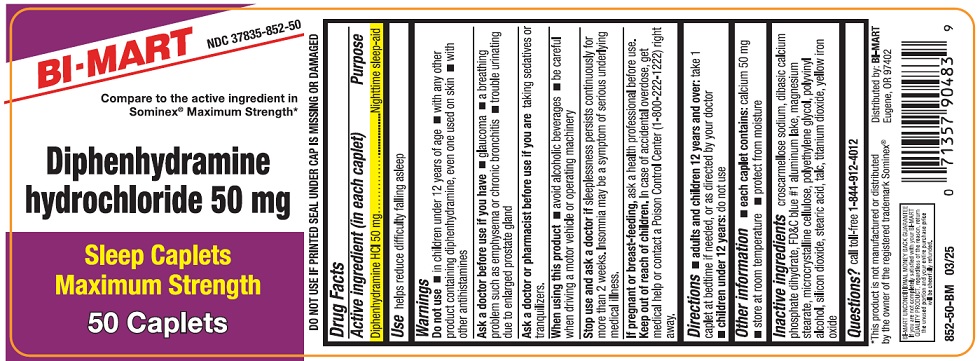 DRUG LABEL: Diphenhydramine HCl

NDC: 37835-852 | Form: TABLET
Manufacturer: Bi-Mart
Category: otc | Type: HUMAN OTC DRUG LABEL
Date: 20250501

ACTIVE INGREDIENTS: DIPHENHYDRAMINE HYDROCHLORIDE 50 mg/1 1
INACTIVE INGREDIENTS: FD&C BLUE NO. 1 ALUMINUM LAKE; CROSCARMELLOSE SODIUM; ANHYDROUS DIBASIC CALCIUM PHOSPHATE; CELLULOSE, MICROCRYSTALLINE; POLYETHYLENE GLYCOL, UNSPECIFIED; MAGNESIUM STEARATE; POLYVINYL ALCOHOL; SILICON DIOXIDE; STEARIC ACID; TALC; TITANIUM DIOXIDE; FERRIC OXIDE YELLOW

Active ingredient (in each caplet)

Diphenhydramine HCl 50 mg

Purpose

Nighttime sleep-aid

Use

helps reduce difficulty falling asleep

Warnings

Do not use

- in children under 12 years of age
- with any other product containing diphenhydramine, even one used on skin
- with other antihistamines

Ask a doctor before use if you have

- glaucoma
- a breathing problem such as emphysema or chronic bronchitis
- trouble urinating due to an enlarged prostate gland

Ask a doctor or pharmacist before use if you are

taking sedatives or tranquilizers.

When using this product

- avoid alcoholic beverages
- be careful when driveing a motor vehicle or operating machinery

Stop use and ask a doctor if

sleeplessness persists continuously for more than 2 weeks. Insomnia may be a symptom of a serious underlying medical illness.

If pregnant or breast-feeding,

ask a health professional before use.

Keep out of reach of children.

In case of accidental overdose, get medical help or contact a Poison Control Center (1-800-222-1222) right away.

Directions

- adults and children 12 years of age and over: take 1 caplet at bedtime if needed, or as directed by your doctor
- children under 12 years: do not use

Other information

- each caplet contains:calcium 50 mg
- store at room temperature
- protect from moisture

Inactive ingredients

colloidal silicon dioxide, croscarmellose sodium, dicalcium calcium phosphate dihydrate, FD&C blue #1 aluminum lake, magnesium stearate, microcrystalline cellulose, polyethylene glycol, polyvinyl alcohol, silicon dioxide, stearic acid, talc, titanium dioxide, yellow iron oxide

Questions?

call toll free 1-844-912-4012

Distributed by:

BI-MART

Eugene, OR 97402